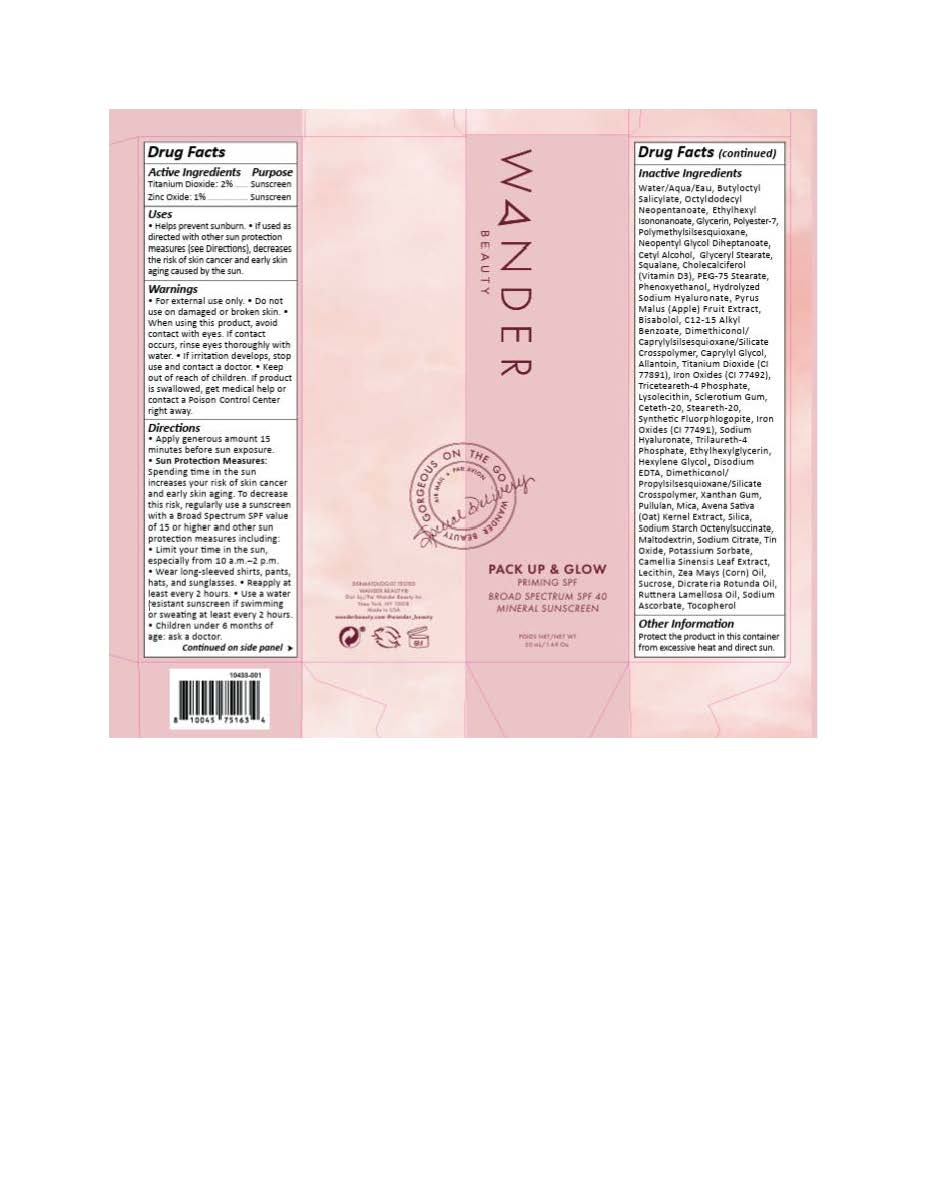 DRUG LABEL: Wander Beauty Pack Up and Glow Priming
NDC: 82510-296 | Form: LOTION
Manufacturer: Wander Beauty
Category: otc | Type: HUMAN OTC DRUG LABEL
Date: 20251114

ACTIVE INGREDIENTS: TITANIUM DIOXIDE 19.4 mg/1 mL; ZINC OXIDE 9.7 mg/1 mL
INACTIVE INGREDIENTS: TOCOPHEROL; OCTYLDODECYL NEOPENTANOATE; PHENOXYETHANOL; POLYESTER-7; TRICETEARETH-4 PHOSPHATE; ETHYLHEXYL ISONONANOATE; HEXYLENE GLYCOL; LECITHIN, SOYBEAN; ALKYL (C12-15) BENZOATE; CAPRYLYL GLYCOL; CETYL ALCOHOL; ETHYLHEXYLGLYCERIN; GLYCERIN; NEOPENTYL GLYCOL DIHEPTANOATE; SILICON DIOXIDE; WATER; XANTHAN GUM; ALLANTOIN; AVENA SATIVA FLOWERING TOP; DIMETHICONOL/PROPYLSILSESQUIOXANE/SILICATE CROSSPOLYMER (450000000 MW); .ALPHA.-BISABOLOL, (+)-; TRILAURETH-4 PHOSPHATE; BUTYLOCTYL SALICYLATE; CETETH-20; PEG-75 STEARATE; PULLULAN; SODIUM CITRATE; SQUALANE; STEARETH-20; FERRIC OXIDE RED; FERRIC OXIDE YELLOW; MICA; SODIUM ASCORBATE

Wander Beauty Pack Up and Glow Priming